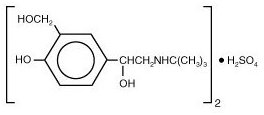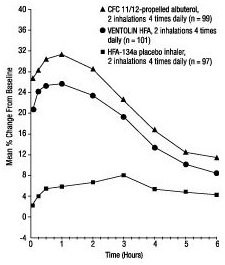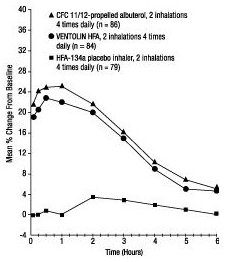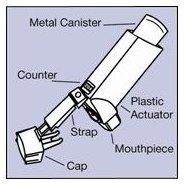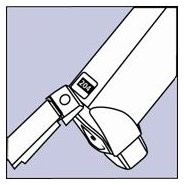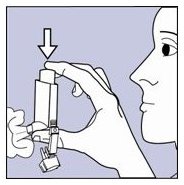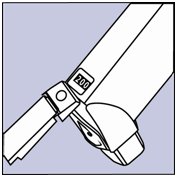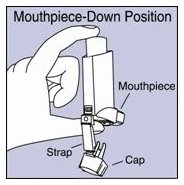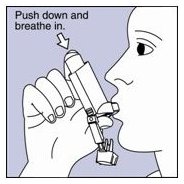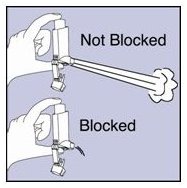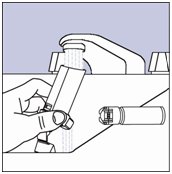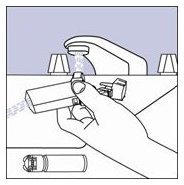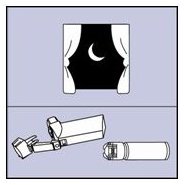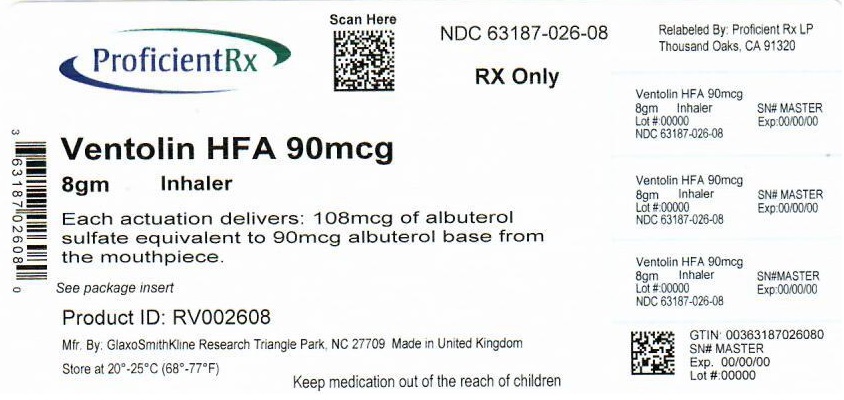 DRUG LABEL: VENTOLIN
NDC: 63187-026 | Form: AEROSOL, METERED
Manufacturer: Proficient Rx LP
Category: prescription | Type: HUMAN PRESCRIPTION DRUG LABEL
Date: 20231001

ACTIVE INGREDIENTS: ALBUTEROL SULFATE 90 ug/1 1
INACTIVE INGREDIENTS: NORFLURANE

HIGHLIGHTS OF PRESCRIBING INFORMATION

These highlights do not include all the information needed to use VENTOLIN HFA safely and effectively. See full prescribing information for VENTOLIN HFA.
VENTOLIN HFA (albuterol sulfate) Inhalation Aerosol
Initial U.S. Approval: 1981

1 INDICATIONS AND USAGE

VENTOLIN HFA is a beta2-adrenergic agonist indicated for:

- Treatment or prevention of bronchospasm in patients 4 years of age and older with reversible obstructive airway disease. (1.1)
- Prevention of exercise-induced bronchospasm in patients 4 years of age and older. (1.2)

2 DOSAGE AND ADMINISTRATION

FOR ORAL INHALATION ONLY.

- Treatment or prevention of bronchospasm in adults and children 4 years of age and older: 2 inhalations every 4 to 6 hours. For some patients, 1 inhalation every 4 hours may be sufficient. (2.1)
- Prevention of exercise-induced bronchospasm in adults and children 4 years of age and older: 2 inhalations 15 to 30 minutes before exercise. (2.2)
- Priming information: Prime VENTOLIN HFA before using for the first time, when the inhaler has not been used for more than 2 weeks, or when the inhaler has been dropped. To prime VENTOLIN HFA, release 4 sprays into the air away from the face, shaking well before each spray. (2.3)
- Cleaning information: At least once a week, wash the actuator with warm water and let it air-dry completely. (2.3)

3 DOSAGE FORMS AND STRENGTHS

Inhalation aerosol: 108 mcg albuterol sulfate (90 mcg albuterol base) from mouthpiece per actuation. Supplied in 18-g canister containing 200 actuations and 8-g canister containing 60 actuations. (3)

4 CONTRAINDICATIONS

Hypersensitivity to albuterol sulfate or any of the ingredients of VENTOLIN HFA. (4)

5 WARNINGS AND PRECAUTIONS

- Paradoxical bronchospasm may occur and should be treated immediately with alternative therapy. (5.1)
- Need for more doses of VENTOLIN HFA than usual may be a sign of deterioration of asthma and requires reevaluation of treatment. (5.2)
- Cardiovascular effects may occur with beta-adrenergic agonists use. Consider discontinuation of VENTOLIN HFA if these effects occur. Use with caution in patients with underlying cardiovascular disorders. (5.4)
- Immediate hypersensitivity reactions may occur. Discontinue VENTOLIN HFA if immediate hypersensitivity reactions occur. (5.6)

6 ADVERSE REACTIONS

Most common adverse reactions (incidence ≥3%) are throat irritation, viral respiratory infections, upper respiratory inflammation, cough, and musculoskeletal pain. (6)

To report SUSPECTED ADVERSE REACTIONS, contact GlaxoSmithKline at 1-888-825-5249 or FDA at 1-800-FDA-1088 or www.fda.gov/medwatch.

7 DRUG INTERACTIONS

- Beta-blockers: May block bronchodilatory effects of beta-agonists and produce severe bronchospasm. Patients with asthma should not normally be treated with beta-blockers. (7.1)
- Diuretics: Electrocardiographic changes and/or hypokalemia associated with diuretics may worsen with concomitant beta-agonists. Consider monitoring potassium levels. (7.2)
- Monoamine oxidase inhibitors (MAOs) or tricyclic antidepressants: May potentiate effect of albuterol on the vascular system. Consider alternative therapy in patients taking MAOs or tricyclic antidepressants. (7.4)

FULL PRESCRIBING INFORMATION

1 INDICATIONS AND USAGE

1.1 Bronchospasm

VENTOLIN® HFA is indicated for the treatment or prevention of bronchospasm in patients 4 years of age and older with reversible obstructive airway disease.

1.2 Exercise-Induced Bronchospasm

VENTOLIN HFA is indicated for the prevention of exercise-induced bronchospasm in patients 4 years of age and older.

2 DOSAGE AND ADMINISTRATION

Administer VENTOLIN HFA by oral inhalation only. Shake VENTOLIN HFA well before each spray.

2.1 Bronchospasm

For treatment of acute episodes of bronchospasm or prevention of symptoms associated with bronchospasm, the usual dosage for adults and children is 2 inhalations repeated every 4 to 6 hours; in some patients, 1 inhalation every 4 hours may be sufficient. More frequent administration or a larger number of inhalations is not recommended.

2.2 Exercise-Induced Bronchospasm

The usual dosage for adults and children 4 years of age and older is 2 inhalations 15 to 30 minutes before exercise.

2.3 Administration Information

Priming: Priming VENTOLIN HFA is essential to ensure appropriate albuterol content in each actuation. Prime VENTOLIN HFA before using for the first time, when the inhaler has not been used for more than 2 weeks, or when the inhaler has been dropped. To prime VENTOLIN HFA, release 4 sprays into the air away from the face, shaking well before each spray.

Cleaning: To ensure proper dosing and to prevent actuator orifice blockage, wash the actuator with warm water and let it air-dry completely at least once a week.

Dose Counter: VENTOLIN HFA has a dose counter attached to the canister that starts at 204 or 64 and counts down each time a spray is released [see Dosage Forms and Strengths (3)]. When the counter reads 020, the patient should contact the pharmacist for a refill of medication or consult the physician to determine whether a prescription refill is needed.

VENTOLIN HFA comes in a moisture-protective foil pouch, which should be removed prior to use. Discard VENTOLIN HFA when the counter reads 000 or 12 months after removal from the moisture-protective foil pouch, whichever comes first [see Dosage Forms and Strengths (3)].

See Patient Information tear-off leaflet for instructions on how to prime and clean the inhaler to ensure proper dosing and to prevent actuator orifice blockage.

3 DOSAGE FORMS AND STRENGTHS

VENTOLIN HFA is an inhalation aerosol. Each actuation contains 108 mcg albuterol sulfate (90 mcg albuterol base) from the mouthpiece. VENTOLIN HFA is supplied as an 18-g pressurized aluminum canister with dose counter fitted with a blue plastic actuator and a blue strapcap; this canister contains 200 actuations. VENTOLIN HFA is also supplied as an 8-g pressurized aluminum canister with dose counter fitted with a blue plastic actuator and a blue strapcap; this canister contains 60 actuations.

4 CONTRAINDICATIONS

VENTOLIN HFA is contraindicated in patients with a history of hypersensitivity to albuterol or any other components of VENTOLIN HFA. Rare cases of hypersensitivity reactions, including urticaria, angioedema, and rash have been reported after the use of albuterol sulfate.

5 WARNINGS AND PRECAUTIONS

5.1 Paradoxical Bronchospasm

Inhaled albuterol sulfate can produce paradoxical bronchospasm, which may be life threatening. If paradoxical bronchospasm occurs, VENTOLIN HFA should be discontinued immediately and alternative therapy instituted. It should be recognized that paradoxical bronchospasm, when associated with inhaled formulations, frequently occurs with the first use of a new canister.

5.2 Deterioration of Asthma

Asthma may deteriorate acutely over a period of hours or chronically over several days or longer. If the patient needs more doses of VENTOLIN HFA than usual, this may be a marker of destabilization of asthma and requires reevaluation of the patient and treatment regimen, giving special consideration to the possible need for anti-inflammatory treatment, e.g., corticosteroids.

5.3 Use of Anti-Inflammatory Agents

The use of beta-adrenergic agonist bronchodilators alone may not be adequate to control asthma in many patients. Early consideration should be given to adding anti-inflammatory agents, e.g., corticosteroids, to the therapeutic regimen.

5.4 Cardiovascular Effects

VENTOLIN HFA, like all other beta2-adrenergic agonists, can produce clinically significant cardiovascular effects in some patients such as changes in pulse rate or blood pressure. If such effects occur, VENTOLIN HFA may need to be discontinued. In addition, beta-agonists have been reported to produce electrocardiogram (ECG) changes, such as flattening of the T wave, prolongation of the QTc interval, and ST segment depression. The clinical relevance of these findings is unknown. Therefore, VENTOLIN HFA, like all other sympathomimetic amines, should be used with caution in patients with underlying cardiovascular disorders, especially coronary insufficiency, cardiac arrhythmias, and hypertension.

5.5 Do Not Exceed Recommended Dose

Fatalities have been reported in association with excessive use of inhaled sympathomimetic drugs in patients with asthma. The exact cause of death is unknown, but cardiac arrest following an unexpected development of a severe acute asthmatic crisis and subsequent hypoxia is suspected.

5.6 Immediate Hypersensitivity Reactions

Immediate hypersensitivity reactions may occur after administration of albuterol sulfate inhalation aerosol, as demonstrated by cases of urticaria, angioedema, rash, bronchospasm, anaphylaxis, and oropharyngeal edema. Discontinue VENTOLIN HFA if immediate hypersensitivity reactions occur.

5.7 Coexisting Conditions

VENTOLIN HFA, like other sympathomimetic amines, should be used with caution in patients with convulsive disorders, hyperthyroidism, or diabetes mellitus and in patients who are unusually responsive to sympathomimetic amines. Large doses of intravenous albuterol have been reported to aggravate preexisting diabetes mellitus and ketoacidosis.

5.8 Hypokalemia

As with other beta-agonists, albuterol may produce significant hypokalemia in some patients, possibly through intracellular shunting, which has the potential to produce adverse cardiovascular effects. The decrease is usually transient, not requiring supplementation.

6 ADVERSE REACTIONS

Use of VENTOLIN HFA may be associated with the following:

- Paradoxical bronchospasm [see Warnings and Precautions (5.1)]
- Cardiovascular effects [see Warnings and Precautions (5.4)]
- Immediate hypersensitivity reactions [see Warnings and Precautions (5.6)]
- Hypokalemia [see Warnings and Precautions (5.8)]

6.1 Clinical Trials Experience

The safety data described below reflects exposure to VENTOLIN HFA in 248 patients treated with VENTOLIN HFA in 3 placebo-controlled clinical trials of 2 to 12 weeks’ duration. The data from adults and adolescents is based upon 2 clinical trials in which 202 patients with asthma 12 years of age and older were treated with VENTOLIN HFA 2 inhalations 4 times daily for 12 weeks’ duration. The adult/adolescent population was 92 female, 110 male and 163 white, 19 black, 18 Hispanic, 2 other. The data from pediatric patients are based upon 1 clinical trial in which 46 patients with asthma 4 to 11 years of age were treated with VENTOLIN HFA 2 inhalations 4 times daily for 2 weeks’ duration. The population was 21 female, 25 male and 25 white, 17 black, 3 Hispanic, 1 other.

Because clinical trials are conducted under widely varying conditions, adverse reaction rates observed in the clinical trials of a drug cannot be directly compared to rates in the clinical trials of another drug and may not reflect the rates observed in practice.

Adults and Adolescents 12 Years of Age and Older: The two 12-week, randomized, double-blind studies in 610 adolescent and adult patients with asthma that compared VENTOLIN HFA, a CFC 11/12-propelled albuterol inhaler, and an HFA-134a placebo inhaler. Overall, the incidence and nature of the adverse reactions reported for VENTOLIN HFA and a CFC 11/12-propelled albuterol inhaler were comparable. Table 1 lists the incidence of all adverse reactions (whether considered by the investigator to be related or unrelated to drug) from these studies that occurred at a rate of 3% or greater in the group treated with VENTOLIN HFA and more frequently in the group treated with VENTOLIN HFA than in the HFA-134a placebo inhaler group.

Table 1. Overall Adverse Reactions With ≥3% Incidence in 2 Large 12-Week Clinical Trials in Adolescents and Adultsa
Adverse Reaction | Percent of Patients
Adverse Reaction | VENTOLIN HFA; (n = 202); % | CFC 11/12-Propelled; Albuterol Inhaler; (n = 207); % | Placebo HFA-134a; (n = 201); %
Ear, nose, and throat
Throat irritation | 10 | 6 | 7
Upper respiratory inflammation | 5 | 5 | 2
Lower respiratory
Viral respiratory infections | 7 | 4 | 4
Cough | 5 | 2 | 2
Musculoskeletal
Musculoskeletal pain | 5 | 5 | 4
aThis table includes all adverse reactions (whether considered by the investigator to be drug-related or unrelated to drug) that occurred at an incidence rate of at least 3.0% in the group treated with VENTOLIN HFA and more frequently in the group treated with VENTOLIN HFA than in the HFA-134a placebo inhaler group.

Adverse reactions reported by less than 3% of the adolescent and adult patients receiving VENTOLIN HFA and by a greater proportion of patients receiving VENTOLIN HFA than receiving HFA-134a placebo inhaler and that have the potential to be related to VENTOLIN HFA include diarrhea, laryngitis, oropharyngeal edema, cough, lung disorders, tachycardia, and extrasystoles. Palpitation and dizziness have also been observed with VENTOLIN HFA.

Pediatric Patients: Results from the 2-week pediatric clinical study in patients with asthma 4 to 11 years of age showed that this pediatric population had an adverse reaction profile similar to that of the adolescent and adult populations.

Three studies have been conducted to evaluate the safety and efficacy of VENTOLIN HFA in patients between birth and 4 years of age. The results of these studies did not establish the efficacy of VENTOLIN HFA in this age-group [see Pediatric Use (8.4)]. Since the efficacy of VENTOLIN HFA has not been demonstrated in children between birth and 48 months of age, the safety of VENTOLIN HFA in this age-group cannot be established. However, the safety profile observed in the pediatric population under 4 years of age was comparable to that observed in the older pediatric patients and in adolescents and adults. Where adverse reaction incidence rates were greater in patients under 4 years of age compared with older patients, the higher incidence rates were noted in all treatment arms, including placebo. These adverse reactions included upper respiratory tract infection, nasopharyngitis, pyrexia, and tachycardia.

6.2 Postmarketing Experience

In addition to the adverse reactions listed in section 6.1, the following adverse reactions have been identified during postapproval use of VENTOLIN HFA. Because these reactions are reported voluntarily from a population of uncertain size, it is not always possible to reliably estimate their frequency or establish a causal relationship to drug exposure.

Cases of paradoxical bronchospasm, hoarseness, arrhythmias (including atrial fibrillation, supraventricular tachycardia), and hypersensitivity reactions (including urticaria, angioedema, rash) have been reported after the use of VENTOLIN HFA.

In addition, albuterol, like other sympathomimetic agents, can cause adverse reactions such as hypokalemia, hypertension, peripheral vasodilatation, angina, tremor, central nervous system stimulation, hyperactivity, sleeplessness, headache, muscle cramps, drying or irritation of the oropharynx, and metabolic acidosis.

7 DRUG INTERACTIONS

Other short-acting sympathomimetic aerosol bronchodilators should not be used concomitantly with albuterol. If additional adrenergic drugs are to be administered by any route, they should be used with caution to avoid deleterious cardiovascular effects.

7.1 Beta-Blockers

Beta-adrenergic receptor blocking agents not only block the pulmonary effect of beta-agonists, such as VENTOLIN HFA, but may produce severe bronchospasm in patients with asthma. Therefore, patients with asthma should not normally be treated with beta-blockers. However, under certain circumstances, e.g., as prophylaxis after myocardial infarction, there may be no acceptable alternatives to the use of beta-adrenergic blocking agents in patients with asthma. In this setting, cardioselective beta-blockers should be considered, although they should be administered with caution.

7.2 Diuretics

The ECG changes and/or hypokalemia that may result from the administration of nonpotassium-sparing diuretics (such as loop or thiazide diuretics) can be acutely worsened by beta-agonists, especially when the recommended dose of the beta-agonist is exceeded. Although the clinical relevance of these effects is not known, caution is advised in the coadministration of beta-agonists with nonpotassium-sparing diuretics. Consider monitoring potassium levels.

7.3 Digoxin

Mean decreases of 16% to 22% in serum digoxin levels were demonstrated after single-dose intravenous and oral administration of albuterol, respectively, to normal volunteers who had received digoxin for 10 days. The clinical relevance of these findings for patients with obstructive airway disease who are receiving inhaled albuterol and digoxin on a chronic basis is unclear. Nevertheless, it would be prudent to carefully evaluate the serum digoxin levels in patients who are currently receiving digoxin and albuterol.

7.4 Monoamine Oxidase Inhibitors or Tricyclic Antidepressants

VENTOLIN HFA should be administered with extreme caution to patients being treated with monoamine oxidase inhibitors or tricyclic antidepressants, or within 2 weeks of discontinuation of such agents, because the action of albuterol on the vascular system may be potentiated. Consider alternative therapy in patients taking MAOs or tricyclic antidepressants.

8 USE IN SPECIFIC POPULATIONS

8.1 Pregnancy

Teratogenic Effects: Pregnancy Category C.

There are no adequate and well-controlled studies of VENTOLIN HFA or albuterol sulfate in pregnant women. During worldwide marketing experience, various congenital anomalies, including cleft palate and limb defects, have been reported in the offspring of patients being treated with albuterol. Some of the mothers were taking multiple medications during their pregnancies. No consistent pattern of defects can be discerned, and a relationship between albuterol use and congenital anomalies has not been established. Animal reproduction studies in mice and rabbits revealed evidence of teratogenicity. VENTOLIN HFA should be used during pregnancy only if the potential benefit justifies the potential risk to the fetus.

In a mouse reproduction study, subcutaneously administered albuterol sulfate produced cleft palate formation in 5 of 111 (4.5%) fetuses at exposures approximately equal to the maximum recommended human dose (MRHD) for adults on a mg/m^2 basis and in 10 of 108 (9.3%) fetuses at approximately 8 times the MRHD. Similar effects were not observed at approximately one eleventh of the MRHD. Cleft palate also occurred in 22 of 72 (30.5%) fetuses from females treated subcutaneously with isoproterenol (positive control).

In a rabbit reproduction study, orally administered albuterol sulfate produced cranioschisis in 7 of 19 fetuses (37%) at approximately 680 times the MRHD.

In another rabbit study, an albuterol sulfate/HFA-134a formulation administered by inhalation produced enlargement of the frontal portion of the fetal fontanelles at approximately one third of the MRHD [see Animal Toxicology and/or Pharmacology (13.2)].

8.2 Labor and Delivery

Because of the potential for beta-agonist interference with uterine contractility, use of VENTOLIN HFA for relief of bronchospasm during labor should be restricted to those patients in whom the benefits clearly outweigh the risk.

8.3 Nursing Mothers

Plasma levels of albuterol sulfate and HFA-134a after inhaled therapeutic doses are very low in humans, but it is not known whether the components of VENTOLIN HFA are excreted in human milk. Because of the potential for tumorigenicity shown for albuterol in animal studies and lack of experience with the use of VENTOLIN HFA by nursing mothers, a decision should be made whether to discontinue nursing or to discontinue the drug, taking into account the importance of the drug to the mother. Caution should be exercised when VENTOLIN HFA is administered to a nursing woman.

8.4 Pediatric Use

The safety and effectiveness of VENTOLIN HFA in children 4 years of age and older has been established based upon two 12-week clinical trials in patients 12 years of age and older with asthma and one 2-week clinical trial in patients 4 to 11 years of age with asthma [see Clinical Studies (14.1), Adverse Reactions (6.1)]. The safety and effectiveness of VENTOLIN HFA in children under 4 years of age has not been established. Three studies have been conducted to evaluate the safety and efficacy of VENTOLIN HFA in patients under 4 years of age and the findings are described below.

Two 4-week randomized, double-blind, placebo-controlled studies were conducted in 163 pediatric patients from birth to 48 months of age with symptoms of bronchospasm associated with obstructive airway disease (presenting symptoms included: wheeze, cough, dyspnea, or chest tightness). VENTOLIN HFA or placebo HFA was delivered with either an AeroChamber Plus® Valved Holding Chamber or an Optichamber® Valved Holding Chamber with mask 3 times daily. In one study, VENTOLIN HFA 90 mcg (N = 26), VENTOLIN HFA 180 mcg (N = 25), and placebo HFA (N = 26) were administered to children between 24 and 48 months of age. In the second study, VENTOLIN HFA 90 mcg (N = 29), VENTOLIN HFA 180 mcg (N = 29), and placebo HFA (N = 28) were administered to children between birth and 24 months of age. Over the 4-week treatment period, there were no treatment differences in asthma symptom scores between the groups receiving VENTOLIN HFA 90 mcg, VENTOLIN HFA 180 mcg, and placebo in either study.

In a third study, VENTOLIN HFA was evaluated in 87 pediatric patients younger than 24 months of age for the treatment of acute wheezing. VENTOLIN HFA was delivered with an AeroChamber Plus Valved Holding Chamber in this study. There were no significant differences in asthma symptom scores and mean change from baseline in an asthma symptom score between VENTOLIN HFA 180 mcg and VENTOLIN HFA 360 mcg.

In vitro dose characterization studies were performed to evaluate the delivery of VENTOLIN HFA via holding chambers with facemasks. The studies were conducted with 2 different holding chambers with facemasks (small and medium size). The in vitro study data when simulated to patients suggest that the dose of VENTOLIN HFA presented for inhalation via a valved holding chamber with facemask will be comparable to the dose delivered in adults without a spacer and facemask per kilogram of body weight (Table 2). However, clinical studies in children under 4 years of age described above suggest that either the optimal dose of VENTOLIN HFA has not been defined in this age-group or VENTOLIN HFA is not effective in this age-group. The safety and effectiveness of VENTOLIN HFA administered with or without a spacer device in children under 4 years of age has not been demonstrated.

Table 2. In Vitro Medication Delivery Through AeroChamber Plus® Valved Holding Chamber With a Facemask
Age | Facemask | Flow Rate (L/min) | Holding Time (seconds) | Mean Medication Delivery Through AeroChamber Plus (mcg/actuation) | Body Weight 50th Percentile (kg)a | Medication Delivered per Actuation (mcg/kg)b
6 to 12 Months | Small | 4.9 | 0; 2; 5; 10 | 18.2; 19.8; 13.8; 15.4 | 7.5-9.9 | 1.8-2.4; 2.0-2.6; 1.4-1.8; 1.6-2.1
2 to 5 Years | Small | 8.0 | 0; 2; 5; 10 | 17.8; 16.0; 16.3; 18.3 | 12.3-18.0 | 1.0-1.4; 0.9-1.3; 0.9-1.3; 1.0-1.5
2 to 5 Years | Medium | 8.0 | 0; 2; 5; 10 | 21.1; 15.3; 18.3; 18.2 | 12.3-18.0 | 1.2-1.7; 0.8-1.2; 1.0-1.5; 1.0-1.5
>5 Years | Medium | 12.0 | 0; 2; 5; 10 | 26.8; 20.9; 19.6; 20.3 | 18.0 | 1.5; 1.2; 1.1; 1.1
aCenters for Disease Control growth charts, developed by the National Center for Health Statistics in collaboration with the National Center for Chronic Disease Prevention and Health Promotion (2000). Ranges correspond to the average of the 50th percentile weight for boys and girls at the ages indicated.
bA single inhalation of VENTOLIN HFA in a 70-kg adult without use of a valved holding chamber and facemask delivers approximately 90 mcg, or 1.3 mcg/kg.

8.5 Geriatric Use

Clinical studies of VENTOLIN HFA did not include sufficient numbers of subjects aged 65 and over to determine whether they respond differently from younger subjects. Other reported clinical experience has not identified differences in responses between the elderly and younger patients. In general, dose selection for an elderly patient should be cautious, usually starting at the low end of the dosing range, reflecting the greater frequency of decreased hepatic, renal, or cardiac function, and of concomitant disease or other drug therapy.

10 OVERDOSAGE

The expected symptoms with overdosage are those of excessive beta-adrenergic stimulation and/or occurrence or exaggeration of any of the symptoms listed under ADVERSE REACTIONS, e.g., seizures, angina, hypertension or hypotension, tachycardia with rates up to 200 beats/min, arrhythmias, nervousness, headache, tremor, dry mouth, palpitation, nausea, dizziness, fatigue, malaise, sleeplessness. Hypokalemia and metabolic acidosis may also occur.

As with all sympathomimetic aerosol medications, cardiac arrest and even death may be associated with abuse of VENTOLIN HFA. Treatment consists of discontinuation of VENTOLIN HFA together with appropriate symptomatic therapy. The judicious use of a cardioselective beta-receptor blocker may be considered, bearing in mind that such medication can produce bronchospasm. There is insufficient evidence to determine if dialysis is beneficial for overdosage of VENTOLIN HFA.

The oral median lethal dose of albuterol sulfate in mice is greater than 2,000 mg/kg (approximately 6,800 times the maximum recommended daily inhalation dose for adults on a mg/m^2 basis and approximately 3,200 times the maximum recommended daily inhalation dose for children on a mg/m^2 basis). In mature rats, the subcutaneous median lethal dose of albuterol sulfate is approximately 450 mg/kg (approximately 3,000 times the maximum recommended daily inhalation dose for adults on a mg/m^2 basis and approximately 1,400 times the maximum recommended daily inhalation dose for children on a mg/m^2 basis). In young rats, the subcutaneous median lethal dose is approximately 2,000 mg/kg (approximately 14,000 times the maximum recommended daily inhalation dose for adults on a mg/m^2 basis and approximately 6,400 times the maximum recommended daily inhalation dose for children on a mg/m^2 basis). The inhalation median lethal dose has not been determined in animals.

11 DESCRIPTION

The active component of VENTOLIN HFA is albuterol sulfate, USP, the racemic form of albuterol and a relatively selective beta2-adrenergic bronchodilator. Albuterol sulfate has the chemical name α^1-[(tert-butylamino)methyl]-4-hydroxy-m-xylene-α, α′-diol sulfate (2:1)(salt) and the following chemical structure:

Albuterol sulfate is a white crystalline powder with a molecular weight of 576.7, and the empirical formula is (C13H21NO3)2•H2SO4. It is soluble in water and slightly soluble in ethanol.

The World Health Organization recommended name for albuterol base is salbutamol.

VENTOLIN HFA is a pressurized metered-dose aerosol unit fitted with a counter. VENTOLIN HFA is intended for oral inhalation only. Each unit contains a microcrystalline suspension of albuterol sulfate in propellant HFA-134a (1,1,1,2-tetrafluoroethane). It contains no other excipients.

Priming VENTOLIN HFA is essential to ensure appropriate albuterol content in each actuation. To prime the inhaler, release 4 sprays into the air away from the face, shaking well before each spray. The inhaler should be primed before using it for the first time, when it has not been used for more than 2 weeks, or when it has been dropped.

After priming, each actuation of the inhaler delivers 120 mcg of albuterol sulfate, USP in 75 mg of suspension from the valve and 108 mcg of albuterol sulfate, USP from the mouthpiece (equivalent to 90 mcg of albuterol base from the mouthpiece).

Each 18-g canister provides 200 inhalations. Each 8-g canister provides 60 inhalations.

This product does not contain chlorofluorocarbons (CFCs) as the propellant.

12 CLINICAL PHARMACOLOGY

12.1 Mechanism of Action

In vitro studies and in vivo pharmacologic studies have demonstrated that albuterol has a preferential effect on beta2-adrenergic receptors compared with isoproterenol. While it is recognized that beta2-adrenergic receptors are the predominant receptors in bronchial smooth muscle, data indicate that there is a population of beta2-receptors in the human heart existing in a concentration between 10% and 50% of cardiac beta-adrenergic receptors. The precise function of these receptors has not been established [see Warnings and Precautions (5.4)].

Activation of beta2-adrenergic receptors on airway smooth muscle leads to the activation of adenylcyclase and to an increase in the intracellular concentration of cyclic-3′,5′-adenosine monophosphate (cyclic AMP). This increase of cyclic AMP leads to the activation of protein kinase A, which inhibits the phosphorylation of myosin and lowers intracellular ionic calcium concentrations, resulting in relaxation. Albuterol relaxes the smooth muscles of all airways, from the trachea to the terminal bronchioles. Albuterol acts as a functional antagonist to relax the airway irrespective of the spasmogen involved, thus protecting against all bronchoconstrictor challenges. Increased cyclic AMP concentrations are also associated with the inhibition of release of mediators from mast cells in the airway.

Albuterol has been shown in most controlled clinical trials to have more effect on the respiratory tract, in the form of bronchial smooth muscle relaxation, than isoproterenol at comparable doses while producing fewer cardiovascular effects. Controlled clinical studies and other clinical experience have shown that inhaled albuterol, like other beta-adrenergic agonist drugs, can produce a significant cardiovascular effect in some patients, as measured by pulse rate, blood pressure, symptoms, and/or electrocardiographic changes [see Warnings and Precautions (5.4)].

12.2 Pharmacokinetics

The systemic levels of albuterol are low after inhalation of recommended doses. A study conducted in 12 healthy male and female subjects using a higher dose (1,080 mcg of albuterol base) showed that mean peak plasma concentrations of approximately 3 ng/mL occurred after dosing when albuterol was delivered using propellant HFA-134a. The mean time to peak concentrations (Tmax) was delayed after administration of VENTOLIN HFA (Tmax = 0.42 hours) as compared to CFC-propelled albuterol inhaler (Tmax = 0.17 hours). Apparent terminal plasma half-life of albuterol is approximately 4.6 hours. No further pharmacokinetic studies for VENTOLIN HFA were conducted in neonates, children, or elderly subjects.

13 NONCLINICAL TOXICOLOGY

13.1 Carcinogenesis, Mutagenesis, Impairment of Fertility

In a 2-year study in Sprague-Dawley rats, albuterol sulfate caused a dose-related increase in the incidence of benign leiomyomas of the mesovarium at and above dietary doses of 2.0 mg/kg (approximately 14 times the maximum recommended daily inhalation dose for adults on a mg/m^2 basis and approximately 6 times the maximum recommended daily inhalation dose for children on a mg/m^2 basis). In another study this effect was blocked by the coadministration of propranolol, a non-selective beta-adrenergic antagonist. In an 18-month study in CD-1 mice, albuterol sulfate showed no evidence of tumorigenicity at dietary doses of up to 500 mg/kg (approximately 1,700 times the maximum recommended daily inhalation dose for adults on a mg/m^2 basis and approximately 800 times the maximum recommended daily inhalation dose for children on a mg/m^2 basis). In a 22-month study in Golden hamsters, albuterol sulfate showed no evidence of tumorigenicity at dietary doses of up to 50 mg/kg (approximately 225 times the maximum recommended daily inhalation dose for adults on a mg/m^2 basis and approximately 110 times the maximum recommended daily inhalation dose for children on a mg/m^2 basis).

Albuterol sulfate was not mutagenic in the Ames test or a mutation test in yeast. Albuterol sulfate was not clastogenic in a human peripheral lymphocyte assay or in an AH1 strain mouse micronucleus assay.

Reproduction studies in rats demonstrated no evidence of impaired fertility at oral doses of albuterol sulfate up to 50 mg/kg (approximately 340 times the maximum recommended daily inhalation dose for adults on a mg/m^2 basis).

13.2 Animal Toxicology and/or Pharmacology

Preclinical: Intravenous studies in rats with albuterol sulfate have demonstrated that albuterol crosses the blood-brain barrier and reaches brain concentrations amounting to approximately 5.0% of the plasma concentrations. In structures outside the blood-brain barrier (pineal and pituitary glands), albuterol concentrations were found to be 100 times those in the whole brain.

Studies in laboratory animals (minipigs, rodents, and dogs) have demonstrated the occurrence of cardiac arrhythmias and sudden death (with histologic evidence of myocardial necrosis) when beta-agonists and methylxanthines are administered concurrently. The clinical relevance of these findings is unknown.

Propellant HFA-134a is devoid of pharmacological activity except at very high doses in animals (380 to 1,300 times the maximum human exposure based on comparisons of AUC values), primarily producing ataxia, tremors, dyspnea, or salivation. These are similar to effects produced by the structurally related CFCs, which have been used extensively in metered-dose inhalers.

In animals and humans, propellant HFA-134a was found to be rapidly absorbed and rapidly eliminated, with an elimination half-life of 3 to 27 minutes in animals and 5 to 7 minutes in humans. Time to maximum plasma concentration (Tmax) and mean residence time are both extremely short, leading to a transient appearance of HFA-134a in the blood with no evidence of accumulation.

Reproductive Toxicology Studies: A study in CD-1 mice given albuterol sulfate subcutaneously showed cleft palate formation in 5 of 111 (4.5%) fetuses at 0.25 mg/kg (less than the maximum recommended daily inhalation dose for adults on a mg/m^2 basis) and in 10 of 108 (9.3%) fetuses at 2.5 mg/kg (approximately 8 times the maximum recommended daily inhalation dose for adults on a mg/m^2 basis). The drug did not induce cleft palate formation at a dose of 0.025 mg/kg (less than the maximum recommended daily inhalation dose for adults on a mg/m^2 basis). Cleft palate also occurred in 22 of 72 (30.5%) fetuses from females treated subcutaneously with 2.5 mg/kg of isoproterenol (positive control).

A reproduction study in Stride Dutch rabbits revealed cranioschisis in 7 of 19 fetuses (37%) when albuterol sulfate was administered orally at a 50 mg/kg dose (approximately 680 times the maximum recommended daily inhalation dose for adults on a mg/m^2 basis).

In an inhalation reproduction study in New Zealand white rabbits, albuterol sulfate/HFA-134a formulation exhibited enlargement of the frontal portion of the fetal fontanelles at and above inhalation doses of 0.0193 mg/kg (less than the maximum recommended daily inhalation dose for adults on a mg/m^2 basis).

A study in which pregnant rats were dosed with radiolabeled albuterol sulfate demonstrated that drug-related material is transferred from the maternal circulation to the fetus.

14 CLINICAL STUDIES

14.1 Bronchospasm Associated With Asthma

Adult and Adolescent Patients 12 Years of Age and Older: The efficacy of VENTOLIN HFA was evaluated in two 12-week, randomized, double-blind, placebo controlled trials in patients 12 years of age and older with mild to moderate asthma. These trials included a total of 610 patients (323 males, 287 females). In each trial, patients received 2 inhalations of VENTOLIN HFA, CFC 11/12-propelled albuterol, or HFA-134a placebo 4 times daily for 12 weeks’ duration. Patients taking the HFA-134a placebo inhaler also took VENTOLIN HFA for asthma symptom relief on an as-needed basis. Some patients who participated in these clinical trials were using concomitant inhaled steroid therapy. Efficacy was assessed by serial forced expiratory volume in 1 second (FEV1). In each of these trials, 2 inhalations of VENTOLIN HFA produced significantly greater improvement in FEV1 over the pretreatment value than placebo. Results from the 2 clinical trials are described below.

In a 12-week, randomized, double-blind study, VENTOLIN HFA (101 patients) was compared to CFC 11/12-propelled albuterol (99 patients) and an HFA-134a placebo inhaler (97 patients) in adolescent and adult patients 12 to 76 years of age with mild to moderate asthma. Serial FEV1 measurements [shown below as percent change from test-day baseline at Day 1 (n = 297) and at Week 12 (n = 249)] demonstrated that 2 inhalations of VENTOLIN HFA produced significantly greater improvement in FEV1 over the pretreatment value than placebo.

FEV1 as Percent Change From Predose in a Large, 12-Week Clinical Trial

Day 1

Week 12

In the responder population (≥15% increase in FEV1 within 30 minutes postdose) treated with VENTOLIN HFA, the mean time to onset of a 15% increase in FEV1 over the pretreatment value was 5.4 minutes, and the mean time to peak effect was 56 minutes. The mean duration of effect as measured by a 15% increase in FEV1 over the pretreatment value was approximately 4 hours. In some patients, duration of effect was as long as 6 hours.

The second 12-week randomized, double-blind study was conducted to evaluate the efficacy and safety of switching patients from CFC 11/12-propelled albuterol to VENTOLIN HFA. During the 3-week run-in phase of the study, all patients received CFC 11/12-propelled albuterol. During the double-blind treatment phase, VENTOLIN HFA (91 patients) was compared to CFC 11/12-propelled albuterol (100 patients) and an HFA-134a placebo inhaler (95 patients) in adolescent and adult patients with mild to moderate asthma. Serial FEV1 measurements demonstrated that 2 inhalations of VENTOLIN HFA produced significantly greater improvement in pulmonary function than placebo. The switching from CFC 11/12-propelled albuterol inhaler to VENTOLIN HFA did not reveal any clinically significant changes in the efficacy profile.

In the 2 adult studies, the efficacy results from VENTOLIN HFA were significantly greater than placebo and were clinically comparable to those achieved with CFC 11/12-propelled albuterol, although small numerical differences in mean FEV1 response and other measures were observed. Physicians should recognize that individual responses to beta-adrenergic agonists administered via different propellants may vary and that equivalent responses in individual patients should not be assumed.

Pediatric Patients 4 Years of Age: The efficacy of VENTOLIN HFA was evaluated in one 2-week, randomized, double-blind, placebo-controlled trial in 135 pediatric patients 4 to 11 years of age with mild to moderate asthma. In this trial, patients received VENTOLIN HFA, CFC 11/12-propelled albuterol, or HFA-134a placebo. Serial pulmonary function measurements demonstrated that 2 inhalations of VENTOLIN HFA produced significantly greater improvement in pulmonary function than placebo and that there were no significant differences between the groups treated with VENTOLIN HFA and CFC 11/12-propelled albuterol. In the responder population treated with VENTOLIN HFA, the mean time to onset of a 15% increase in peak expiratory flow rate (PEFR) over the pretreatment value was 7.8 minutes, and the mean time to peak effect was approximately 90 minutes. The mean duration of effect as measured by a 15% increase in PEFR over the pretreatment value was greater than 3 hours. In some patients, duration of effect was as long as 6 hours.

14.2 Exercise-Induced Bronchospasm

One controlled clinical study in adult patients with asthma (N = 24) demonstrated that 2 inhalations of VENTOLIN HFA taken approximately 30 minutes prior to exercise significantly prevented exercise-induced bronchospasm (as measured by maximum percentage fall in FEV1 following exercise) compared to an HFA-134a placebo inhaler. In addition, VENTOLIN HFA was shown to be clinically comparable to a CFC 11/12-propelled albuterol inhaler for this indication.

16 HOW SUPPLIED/STORAGE AND HANDLING

VENTOLIN HFA (albuterol sulfate) Inhalation Aerosol is supplied in the following packs as a pressurized aluminum canister fitted with a counter with a blue plastic actuator and a blue strapcap packaged within a moisture-protective foil pouch that also contains a desiccant:

NDC 63187-026-08 8-g institutional pack canister containing 60 actuations

Before using, VENTOLIN HFA should be removed from the moisture-protective foil pouch. The pouch and desiccant should be discarded. VENTOLIN HFA should be discarded 12 months after removal from the pouch.

Priming VENTOLIN HFA is essential to ensure appropriate albuterol content in each actuation. To prime the inhaler, release 4 sprays into the air away from the face, shaking well before each spray. The inhaler should be primed before using it for the first time, when the inhaler has not been used for more than 2 weeks, or when it has been dropped.

After priming, each actuation delivers 120 mcg of albuterol sulfate, USP in 75 mg of suspension from the valve and 108 mcg of albuterol sulfate, USP from the mouthpiece (equivalent to 90 mcg of albuterol base from the mouthpiece).

To ensure proper dosing and to prevent actuator orifice blockage, wash the actuator with warm water and let it air-dry completely at least once a week [see the Patient Information tear‑off leaflet].

The blue actuator supplied with VENTOLIN HFA should not be used with any other product canisters, and actuators from other products should not be used with a VENTOLIN HFA canister.

VENTOLIN HFA has a counter attached to the canister. The counter starts at 204 or 64 and counts down each time a spray is released. The correct amount of medication in each inhalation cannot be assured after the counter reads 000, even though the canister is not completely empty and will continue to operate. VENTOLIN HFA should be discarded when the counter reads 000 or 12 months after removal from the moisture-protective foil pouch, whichever comes first. Never immerse the canister in water to determine the amount of drug remaining in the canister.

Keep out of reach of children. Avoid spraying in eyes.

Contents Under Pressure: Do not puncture. Do not use or store near heat or open flame. Exposure to temperatures above 120°F may cause bursting. Never throw container into fire or incinerator.

Store between 15° and 25°C (59° and 77°F). Store the inhaler with the mouthpiece down. For best results, the inhaler should be at room temperature before use. SHAKE WELL BEFORE EACH SPRAY.

VENTOLIN HFA does not contain chlorofluorocarbons (CFCs) as the propellant.

17 PATIENT COUNSELING INFORMATION

See FDA-approved patient labeling (Patient Information and Instructions for Use).

17.1 Frequency of Use

The action of VENTOLIN HFA should last up to 4 to 6 hours. VENTOLIN HFA should not be used more frequently than recommended. Do not increase the dose or frequency of doses of VENTOLIN HFA without consulting the physician. If patients find that treatment with VENTOLIN HFA becomes less effective for symptomatic relief, symptoms become worse, and/or they need to use the product more frequently than usual, they should seek medical attention immediately.

17.2 Priming and Cleaning

Priming: Patients should be instructed that priming VENTOLIN HFA is essential to ensure appropriate albuterol content in each actuation. Patients should prime VENTOLIN HFA before using for the first time, when the inhaler has not been used for more than 2 weeks, or when the inhaler has been dropped. To prime VENTOLIN HFA, patients should release 4 sprays into the air away from the face, shaking well before each spray.

Cleaning: To ensure proper dosing and to prevent actuator orifice blockage, patients should be instructed to wash the actuator and dry thoroughly at least once a week. Patients should be informed that detailed cleaning instructions are included in the Patient Information leaflet.

17.3 Dose Counter

Patients should be informed that VENTOLIN HFA has a dose counter that starts at 204 or 64 and counts down each time a spray is released. Patients should be informed to discard VENTOLIN HFA when the counter reads 000 or 12 months after removal from the moisture-protective foil pouch, whichever comes first. When the counter reads 020, the patient should contact the pharmacist for a refill of medication or consult the physician to determine whether a prescription refill is needed. Patients should never try to alter the numbers or remove the counter from the metal canister. Patients should never immerse the canister in water to determine the amount of drug remaining in the canister.

17.4 Paradoxical Bronchospasm

Patients should be informed that VENTOLIN HFA can produce paradoxical bronchospasm. If paradoxical bronchospasm occurs, patients should discontinue VENTOLIN HFA.

17.5 Concomitant Drug Use

While patients are using VENTOLIN HFA, other inhaled drugs and asthma medications should be taken only as directed by the physician.

17.6 Common Adverse Effects

Common adverse effects of treatment with inhaled albuterol include palpitations, chest pain, rapid heart rate, tremor, and nervousness.

17.7 Pregnancy

Patients who are pregnant or nursing should contact their physicians about the use of VENTOLIN HFA.

VENTOLIN is a registered trademark of GlaxoSmithKline.

AeroChamber Plus is a registered trademark of Monaghan Medical Inc.

OptiChamber is a registered trademark of Respironics Inc.

GlaxoSmithKline
Research Triangle Park, NC 27709

©2012, GlaxoSmithKline. All rights reserved.

VNT:8PI

PHARMACIST—DETACH HERE AND GIVE LEAFLET TO PATIENT

Patient Information

VENTOLIN® HFA (vent′ o-lin)

(albuterol sulfate)

Inhalation Aerosol

Read this Patient Information before you start using VENTOLIN HFA and each time you get a refill. There may be new information. This information does not take the place of talking to your healthcare provider about your medical condition or your treatment.

What is VENTOLIN HFA?

VENTOLIN HFA is a prescription medicine used in people 4 years of age and older to:

- treat or prevent bronchospasm in people who have reversible obstructive airway disease
- prevent exercise-induced bronchospasm

It is not known if VENTOLIN HFA is safe and effective in children under 4 years of age.

Who should not use VENTOLIN HFA?

Do not use VENTOLIN HFA if you are allergic to albuterol sulfate or any of the ingredients in VENTOLIN HFA. See the end of this Patient Information leaflet for a complete list of ingredients in VENTOLIN HFA.

What should I tell my healthcare provider before I use VENTOLIN HFA?

Before you use VENTOLIN HFA, tell your healthcare provider if you:

- have heart problems
- have high blood pressure (hypertension)
- have convulsions (seizures)
- have thyroid problems
- have diabetes
- have low potassium levels in your blood
- are pregnant or plan to become pregnant. It is not known if VENTOLIN HFA will harm your unborn baby. Talk to your healthcare provider if you are pregnant or plan to become pregnant.
- are breastfeeding or plan to breastfeed. It is not known if VENTOLIN HFA passes into your breast milk. Talk to your healthcare provider about the best way to feed your baby if you are using VENTOLIN HFA.

Tell your healthcare provider about all the medicines you take, including prescription and nonprescription medicines, vitamins, and herbal supplements.

VENTOLIN HFA and other medicines may affect each other and cause side effects. VENTOLIN HFA may affect the way other medicines work, and other medicines may affect the way VENTOLIN HFA works.

Especially tell your healthcare provider if you take:

- other inhaled medicines or asthma medicines
- beta-blocker medicines
- diuretics
- digoxin
- monoamine oxidase inhibitors
- tricyclic antidepressants

Ask your healthcare provider or pharmacist for a list of these medicines if you are not sure.

Know the medicines you take. Keep a list of them to show your healthcare provider and pharmacist when you get a new medicine.

How should I use VENTOLIN HFA?

- For detailed instructions, see “Instructions for Use” at the end of this Patient Information.
- Use VENTOLIN HFA exactly as your healthcare provider tells you to use it.
- Do not increase your dose or take extra doses of VENTOLIN HFA without first talking to your healthcare provider.
- If your child needs to use VENTOLIN HFA, watch your child closely to make sure your child uses the inhaler correctly. Your healthcare provider will show you how your child should use VENTOLIN HFA.
- Each dose of VENTOLIN HFA should last up to 4 hours to 6 hours.
- Get medical help right away if VENTOLIN HFA no longer helps your symptoms.
- Get medical help right away if your symptoms get worse or if you need to use your inhaler more often.
- While you are using VENTOLIN HFA, use other inhaled medicines and asthma medicines only as directed by your healthcare provider.
- Call your healthcare provider if your asthma symptoms like wheezing and trouble breathing become worse over a few hours or days. Your healthcare provider may need to give you another medicine to treat your symptoms.

What are the possible side effects of VENTOLIN HFA?

VENTOLIN HFA may cause serious side effects, including:

- worsening trouble breathing, coughing, and wheezing (paradoxical bronchospasm). If this happens, stop using VENTOLIN HFA and call your healthcare provider or get emergency help right away. Paradoxical bronchospasm is more likely to happen with your first use of a new canister of medicine.
- heart problems, including faster heart rate and higher blood pressure
- possible death in people with asthma who use too much VENTOLIN HFA
- allergic reactions. Call your healthcare provider right away if you have any of the following symptoms of an allergic reaction:
  - itchy skin
  - swelling beneath your skin or in your throat
  - rash
  - worsening trouble breathing
- low potassium levels in your blood
- worsening of other medical problems in people who also use VENTOLIN HFA, including increases in blood sugar

Common side effects of VENTOLIN HFA include:

- your heart feels like it is pounding or racing (palpitations)
- chest pain
- fast heart rate
- shakiness
- nervousness
- headache
- pain
- dizziness
- sore throat
- runny nose

Tell your healthcare provider if you have any side effect that bothers you or that does not go away.

These are not all the possible side effects of VENTOLIN HFA. For more information, ask your healthcare provider or pharmacist.

Call your doctor for medical advice about side effects. You may report side effects to FDA at 1-800-FDA-1088.

How should I store VENTOLIN HFA?

- Store VENTOLIN HFA at room temperature between 59°F and 77°F (15°C and 25°C) with the mouthpiece down.
- Avoid exposure to extreme heat and cold.
- Shake the VENTOLIN HFA canister well before use.
- Do not puncture the VENTOLIN HFA canister.
- Do not store the VENTOLIN HFA canister near heat or a flame. Temperatures above 120°F may cause the canister to burst.
- Do not throw the VENTOLIN HFA canister into a fire or an incinerator.
- Avoid spraying VENTOLIN HFA in your eyes.

Keep VENTOLIN HFA and all medicines out of the reach of children.

General information about the safe and effective use of VENTOLIN HFA

Medicines are sometimes prescribed for purposes other than those listed in a Patient Information leaflet. Do not use VENTOLIN HFA for a condition for which it was not prescribed. Do not give VENTOLIN HFA to other people, even if they have the same symptoms that you have. It may harm them.

This Patient Information leaflet summarizes the most important information about VENTOLIN HFA. If you would like more information, talk with your healthcare provider. You can ask your pharmacist or healthcare provider for information about VENTOLIN HFA that is written for healthcare professionals.

For more information, go to www.ventolin.com or call 1-888-825-5249.

What are the ingredients in VENTOLIN HFA?

Active ingredient: albuterol sulfate

Inactive ingredient: propellant HFA-134a

Instructions for Use

VENTOLIN® HFA (vent′ o-lin)

(albuterol sulfate)

Inhalation Aerosol

Read this Instructions for Use before you start using VENTOLIN HFA and each time you get a refill. There may be new information. This information does not take the place of talking to your healthcare provider about your medical condition or your treatment.

The parts of your VENTOLIN HFA inhaler:

There are 2 main parts of your VENTOLIN HFA inhaler:

- the blue plastic actuator that sprays the medicine into your mouth. See Figure A.
- the metal canister that holds the medicine. See Figure A.

Figure A

The actuator has a protective cap that covers the mouthpiece. The strap on the cap will stay attached to the actuator.

Do not use this actuator with a canister of medicine from any other inhaler.

Do not use this canister of medicine with an actuator from any other inhaler.

The canister has a counter that shows you how many sprays of medicine you have left. The number shows through a window in the back of the actuator. The counter starts at either 204 or 64, depending on which size inhaler you have. See Figure B.

Figure B

Priming your VENTOLIN HFA inhaler:

Your VENTOLIN HFA inhaler must be primed before you use it for the first time, when it has not been used for more than 14 days in a row, or if it has been dropped. Do not prime your VENTOLIN HFA every day.

- Remove your VENTOLIN HFA inhaler from its packaging.
- Throw away the pouch and the drying packet that comes inside the pouch.
- Remove the protective cap from the mouthpiece.
- Shake the inhaler well, and spray it into the air away from your face. See Figure C.

Figure C

- Shake and spray the inhaler like this 3 more times to finish priming it. After you prime the actuator for the first time, the dose counter in the window on the back of the actuator should show the number 200 or 60, depending on which size inhaler you have. See Figure D.

Figure D

Each time you use your VENTOLIN HFA inhaler:

- Make sure the canister fits firmly in the plastic actuator.
- Look into the mouthpiece to make sure there are no foreign objects there, especially if the strap is no longer attached to the actuator or the cap has not been used to cover the mouthpiece.

Reading the dose counter on your VENTOLIN HFA actuator:

- The dose counter will count down by 1 number each time you spray the inhaler.
- The dose counter stops counting when it reaches 000. It will continue to show 000.
- The dose counter cannot be reset, and it is permanently attached to the metal canister. Never try to change the numbers for the dose counter or take the counter off the metal canister.
- Do not remove the canister from the plastic actuator except during cleaning to prevent accidently spraying a dose of VENTOLIN HFA into the air.

Using your VENTOLIN HFA inhaler:

Step 1.Shake the inhaler well before each spray. Take the cap off the mouthpiece of the actuator.

Step 2. Hold the inhaler with the mouthpiece down. See Figure E.

Figure E

Step 3. Breathe out through your mouth and push as much air from your lungs as you can. Put the mouthpiece in your mouth and close your lips around it. See Figure F.

Figure F

Step 4. Push the top of the canister all the way down while you breathe in deeply and slowly through your mouth. See Figure F.

Step 6.Hold your breath as long as you can, up to 10 seconds, then breathe normally.

If your healthcare provider has told you to use more sprays, wait 1 minute and shake the inhaler again. Repeat Steps 2 through Step 6.

Step 7. Put the cap back on the mouthpiece after every time you use the inhaler. Make sure the cap snaps firmly into place.

Cleaning your VENTOLIN HFA actuator:

It is very important to keep the plastic actuator clean so the medicine will not build-up and block the spray. See Figure G.

Figure G

- Do not try to clean the metal canister or let it get wet. The inhaler may stop spraying if it is not cleaned correctly.
- Wash the actuator at least once a week as follows:
Step 8. Take the canister out of the actuator, and take the cap off the mouthpiece. The strap on the cap will stay attached to the actuator.

Figure H

Step 10. Turn the actuator upside down and run warm water through the mouthpiece for about 30 seconds. See Figure I.

Figure I

Step 11. Shake off as much water from the actuator as you can. Look into the mouthpiece to make sure any medicine build-up has been completely washed away. If there is any build-up, repeat Steps 9 and 10.

Figure J

Step 13. When the actuator is dry, put the canister in the actuator and make sure it fits firmly. Shake the inhaler well and spray it once into the air away from your face. (The counter will count down by 1 number.) Put the cap back on the mouthpiece.

If you need to use your inhaler before the actuator is completely dry:

- Shake as much water off the actuator as you can.
- Put the canister in the actuator and make sure it fits firmly.
- Shake the inhaler well and spray it once into the air away from your face.
- Take your VENTOLIN HFA dose as prescribed.
- Follow cleaning Steps 8 through 13 above.

Replacing your VENTOLIN HFA inhaler:

- When the dose counter on the actuator shows the number 020, you need to refill your prescription or ask your doctor for another prescription for VENTOLIN HFA.
- Throw the VENTOLIN HFA inhaler away as soon as the dose counter shows 000, after the expiration date on the VENTOLIN HFA packaging, or 12 months after you open the foil pouch, whichever comes first. You should not keep using the inhaler after the dose counter shows 000 even though the canister may not be completely empty. You cannot be sure you will receive the right amount of medicine.

VENTOLIN is a registered trademark of GlaxoSmithKline.

This Patient Information and Instructions for Use has been approved by the U.S. Food and Drug Administration.

GlaxoSmithKline

Research Triangle Park, NC 27709

©2012, GlaxoSmithKline. All rights reserved.

October 2012

VNT:8PIL

Relabeled by:

Proficient Rx LP

Thousand Oaks, CA 91320